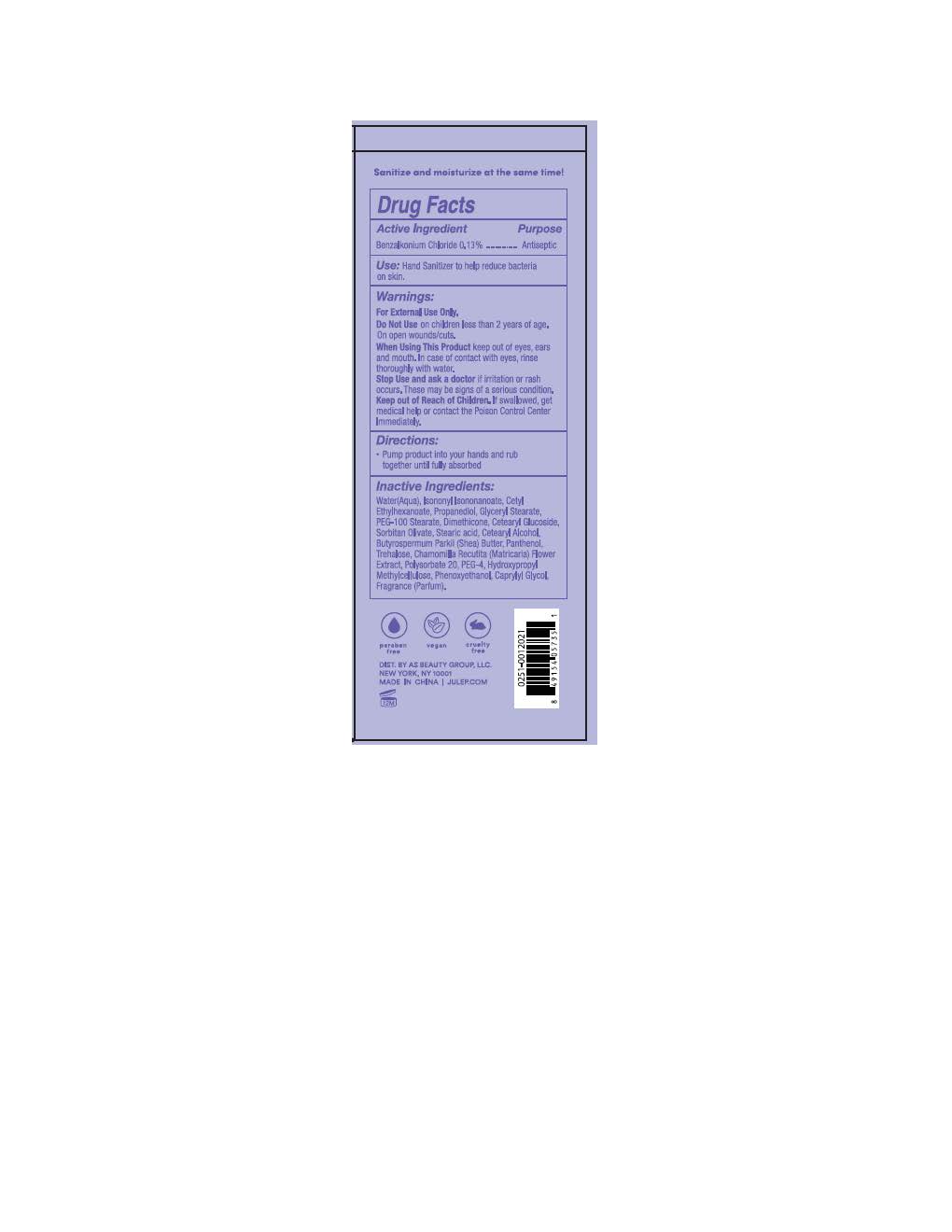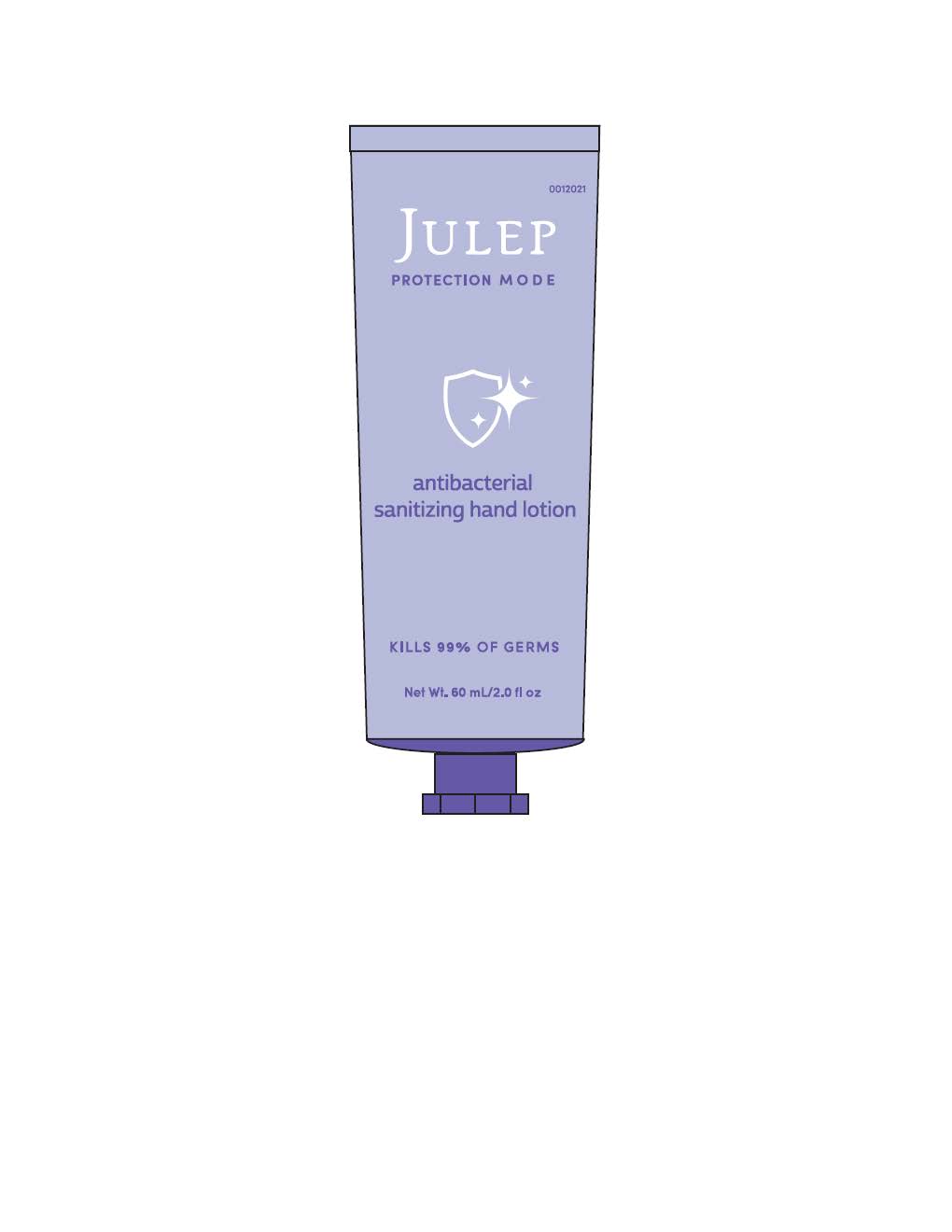 DRUG LABEL: Antibacterial
NDC: 74884-301 | Form: LOTION
Manufacturer: AS Beauty
Category: otc | Type: HUMAN OTC DRUG LABEL
Date: 20201021

ACTIVE INGREDIENTS: BENZALKONIUM CHLORIDE 0.13 g/0.13 g
INACTIVE INGREDIENTS: STEARIC ACID; PROPANEDIOL; POLYETHYLENE GLYCOL 200; TREHALOSE; GLYCERYL STEARATE/PEG-100 STEARATE; WATER; POLYSORBATE 20; FRAGRANCE FLORAL ORC0902236; CHAMOMILE; DIMETHICONE; CETEARYL GLUCOSIDE; SHEA BUTTER; SORBITAN OLIVATE; CAPRYLYL GLYCOL; PHENOXYETHANOL; ISONONYL ISONONANOATE; CETYL ETHYLHEXANOATE; HYPROMELLOSE, UNSPECIFIED; PANTHENOL; CETOSTEARYL ALCOHOL

Antibacterial Lotion

DOSAGE AND ADMINISTRATION

Pump product into hands and rub thoroughly until completely absorbed.

INACTIVE INGREDIENT

Water, Isononyl Isononanoate, Cetyl Ethylhexanoate, Propanediol, Glyceryl Stearate, PEG-100 Stearate, Dimethicone, Cetearyl Glucoside, Sorbitan Olivate, Stearic Acid, Cetearyl Alcohol. Butyrospermum Parkii (Shea) Butter, Panthenol, Trehalose, Chamomilla Recutita (Matricaria) Flower Extract, Polysorbate 20, PEG-4, Hydroxypropyl Methylcellulose, Phenoxyethanol, Caprylyl Glycol, Fragrance (Parfum

INDICATIONS AND USAGE

If rash or irritation occurs, stop using. Consult a physician if the condition worsens.

Keep Out Of Reach Of Children

PURPOSE

Antibacterial

WARNINGS

For external use only. Do not use on cuts or open wounds.